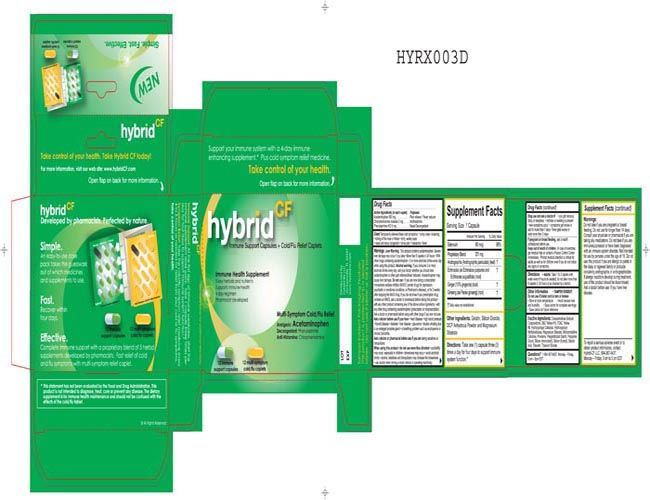 DRUG LABEL: hybrid CF
NDC: 49804-101 | Form: TABLET, FILM COATED
Manufacturer: Hybrid-Rx LLC
Category: otc | Type: HUMAN OTC DRUG LABEL
Date: 20100203

ACTIVE INGREDIENTS: ACETAMINOPHEN 500 mg/1 1; PHENYLEPHRINE HYDROCHLORIDE 5 mg/1 1; CHLORPHENIRAMINE MALEATE 2 mg/1 1
INACTIVE INGREDIENTS: D&C YELLOW NO. 10; FD&C YELLOW NO. 6; HYPROMELLOSE 2910 (15 CPS); TRIACETIN; POVIDONE; STEARIC ACID; CELLULOSE, MICROCRYSTALLINE

Drug Facts

Active Ingredients (in each caplet)
Acetaminophen 500 mg
Chlorpheniramine maleate 2 mg
Phenylephrine HCl 5 mg

Purposes
Pain reliever/Fever Reducer
Antihistamine
Nasal Decongestant

Directions

Adults: Take 1 to 2 caplets with water every 6 hours as needed; do not take more than 8 caplets in 24 hours or as directed by a doctor.

INACTIVE INGREDIENT

Enter section text here

QUESTIONS

Questions? 1-904-367-8437, Monday-Friday, 9am-5pm EST

Warnings

Liver warning: This product contains acetaminophen. Severe liver damage may occur if you take

more than 8 caplets in 24 hours

with other drugs containing acetaminophen

3 or more alcoholic drinks every day while using this product

Alcohol warning: If you consume 3 or more alcoholic drinks every day, ask your doctor whether you should take acetaminophen or other pain relievers/fever reducers. Acetaminophen may cause liver damage.

Do Not Use

- if you are now taking a prescription monoamine oxidase inhibitor (MAOI) (certain drugs for depression, psychiatric or emotional conditions, or Parkinson's disease), or for 2 weeks after stopping the MAOI drug. If you do not know if your prescription drug contains an MAOI, ask a doctor or pharmacist before taking this product

- with any other product containing any of the above active ingredients.

- with any other drug containing acetaminophen (prescription or nonprescription).

- Ask a doctor or pharmacist before using with other drugs if you are not sure.

Ask a doctor before use if you have

- liver disease
- heart disease
- high blood pressure
- thyroid disease
- diabetes
- glaucoma
- trouble urinating due to an enlarged prostate gland
- a breathing problem such as emphysema or chronic bronchitis

Ask a doctor or pharmacist before use if

you are taking sedatives or tranquilizers.

When using this product

- do not use more than directed

- excitability may occur, especially in children

- drowsiness may occur

- avoid alcoholic drinks

- alcohol, sedatives and tranquilizers may increase the drowsiness

- use caution when driving a motor vehicle or operating machinery

Stop use and ask a doctor if

- you get nervous, dizzy or sleepless
- redness of swelling is present
- new symptoms occur
- symptoms get worse or last for more than 7 days
- fever gets worse or lasts more than 3 days

If pregnant or breast feeding

ask a health professional before use.

Keep out of reach of children

In case of overdose, get medical help or contact a Poison Control Center immediately. Prompt medical attention is critical for adults as well as for children even if you do not notice any signs or symptoms.

Hybrid CF

aada0b4d-1776-48e5-98e2-a2e769279c5a.jpg